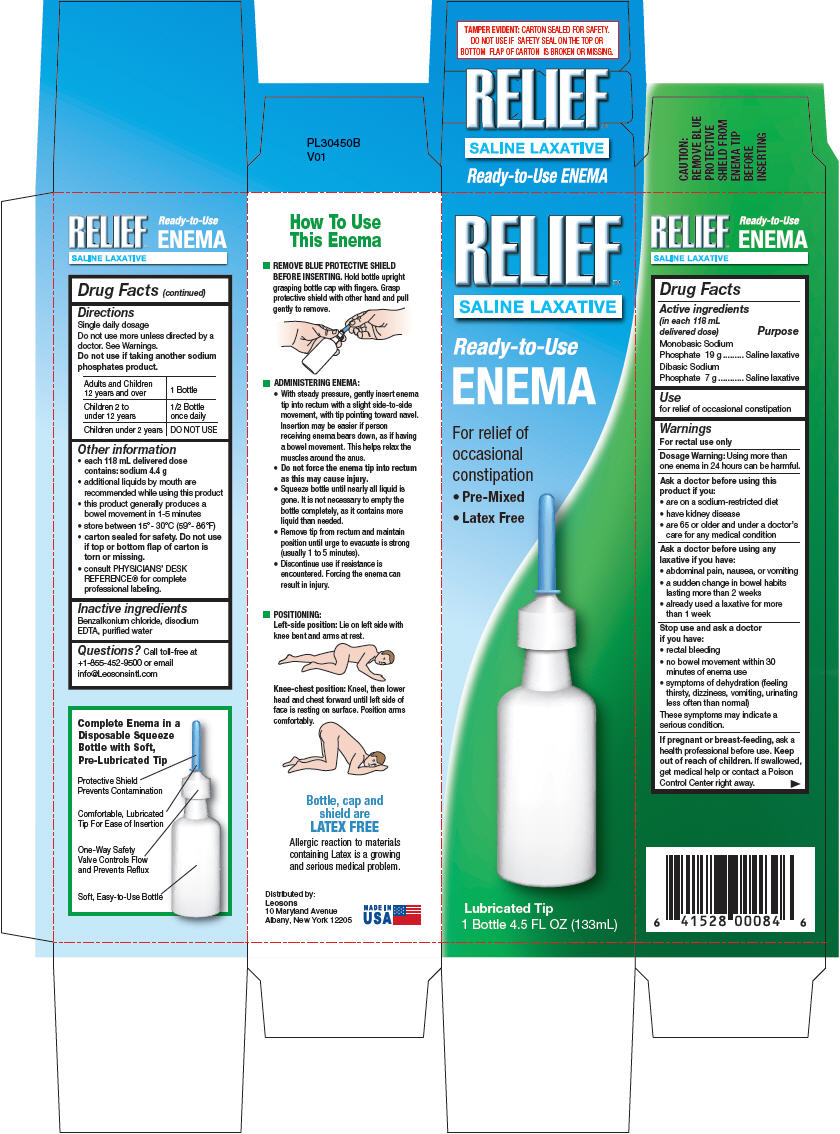 DRUG LABEL: Relief
NDC: 69626-0084 | Form: ENEMA
Manufacturer: Leosons Overseas Corp
Category: otc | Type: HUMAN OTC DRUG LABEL
Date: 20241119

ACTIVE INGREDIENTS: SODIUM PHOSPHATE, MONOBASIC 19 g/133 mL; SODIUM PHOSPHATE, DIBASIC, HEPTAHYDRATE 7 g/133 mL
INACTIVE INGREDIENTS: BENZALKONIUM CHLORIDE; EDETATE DISODIUM; WATER

Relief Saline Laxative 4.5 fl oz

Drug Facts

Active ingredients & Purpose

PURPOSE

Active ingredients (in each 118 mL delivered dose) | Purpose
Monobasic Sodium Phosphate 19 g............................................... | Saline laxative
Dibasic Sodium Phosphate 7 g....................................................... | Saline laxative

Use

for relief of occasional constipation

Warnings

For rectal use only

Dosage Warning:

Using more than one enema in 24 hours can be harmful.

Ask a doctor before using this product if you

- are on a sodium-restricted diet
- have kidney disease
- are 65 or older and under a doctor's care for any medical condition

Ask a doctor before using any laxative if you have

- abdominal pain, nausea, or vomiting
- a sudden change in bowel habits lasting more than 2 weeks
- already used a laxative for more than 1 week

Stop use and ask a doctor if you have

- rectal bleeding
- no bowel movement within 30 minutes of enema use
- symptoms of dehydration (feeling thirsty, dizziness, vomiting, urinating less often than normal)

These symptoms may indicate a serious condition.

If pregnant or breast-feeding,

ask a health professional before use.

Keep out of reach of children.

If swallowed, get medical help or contact a Poison Control Center right away.

Directions

- Single daily dosage.
- Do not use more unless directed by a doctor. See Warnings.
- Do not use if taking another sodium phosphates product.

Adults and Children 12 years and over | 1 Bottle
Children 2 to under 12 years | 1/2 Bottle once daily
Children under 2 years | DO NOT USE

Other information

- each 118 mL delivered dose contains: sodium 4.4 g
- additional liquids by mouth are recommended while using this product
- this product generally produces a bowel movement in 1-5 minutes
- store between 15°- 30°C (59°- 86°F)
- carton sealed for safety. Do not use if top or bottom flap of carton is torn or missing.
- consult PHYSICIANS' DESK REFERENCE® for complete professional labeling.

Inactive ingredients

Benzalkonium chloride, disodium EDTA, purified water

Questions?

Call toll-free at +1-855-452-9500 or email info@Leosonsintl.com

Distributed by:

Leosons
10 Maryland Avenue
Albany, New York 12205

PRINCIPAL DISPLAY PANEL - 133 mL Bottle Carton

RELIEF™

SALINE LAXATIVE

Ready-to-Use
ENEMA

For relief of
occasional
constipation

- Pre-Mixed
- Latex Free

Lubricated Tip
1 Bottle 4.5 FL OZ (133mL)